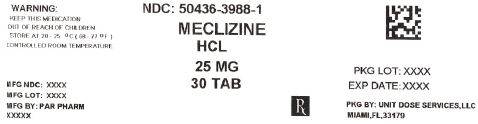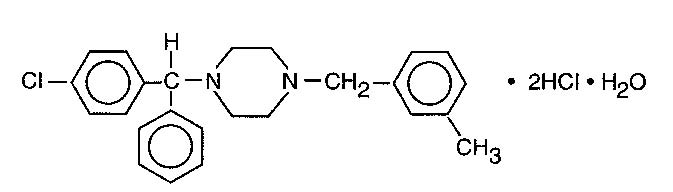 DRUG LABEL: Meclizine Hydrochloride
NDC: 50436-3988 | Form: TABLET
Manufacturer: Unit Dose Services
Category: prescription | Type: HUMAN PRESCRIPTION DRUG LABEL
Date: 20171107

ACTIVE INGREDIENTS: MECLIZINE HYDROCHLORIDE 25 mg/1 1
INACTIVE INGREDIENTS: ANHYDROUS LACTOSE; MICROCRYSTALLINE CELLULOSE; SODIUM STARCH GLYCOLATE TYPE A POTATO; STARCH, CORN; STEARIC ACID; WATER; ISOPROPYL ALCOHOL; D&C YELLOW NO. 10; MAGNESIUM STEARATE; SILICON DIOXIDE; FD&C YELLOW NO. 5

Rx Only

DESCRIPTION

Meclizine hydrochloride, an oral antiemetic, is a white, slightly yellowish, crystalline powder which has a slight odor and is tasteless. It has the following structural formula:

C25H27CIN2•2HCI•H2O M.W. 481.89

The chemical name is 1-(p-chloro-alpha-phenylbenzyl)-4-(m-methyl-benzyl) - piperazine dihydrochloride monohydrate.

Meclizine Hydrochloride Tablets are available in 12.5 mg, and *25 mg strengths for oral administration.

*Contains FD&C Yellow #5 (see PRECAUTIONS).

Each tablet contains the following inactive ingredients: colloidal silicon dioxide, lactose, magnesium stearate, microcrystalline cellulose, sodium starch glycolate, starch, and stearic acid. In addition, the 12.5 mg tablet contains FD&C Blue #1; and the 25 mg tablet contains D&C Yellow #10 and FD&C Yellow #5.

CLINICAL PHARMACOLOGY

Meclizine hydrochloride is an antihistamine which shows marked protective activity against nebulized histamine and lethal doses of intravenously injected histamine in guinea pigs. It has a marked effect in blocking the vasodepressor response to histamine, but only a slight blocking action against acetylcholine. Its activity is relatively weak in inhibiting the spasmogenic action of histamine on isolated guinea pig ileum.

Pharmacokinetics

The available pharmacokinetic information for meclizine following oral administration has been summarized from published literature.

Absorption

Meclizine is absorbed after oral administration with maximum plasma concentrations reaching at a median Tmax value of 3 hours post-dose (range: 1.5 to 6 hours) for the tablet dosage form.

Distribution

Drug distribution characteristics for meclizine in humans in unknown.

Metabolism

The metabolic fate of meclizine in humans in unknown. In an in vitro metabolic study using human hepatic microsome and recombinant CYP enzyme, CYP2D6 was found to be the dominant enzyme for metabolism of meclizine.

The genetic polymorphism of CYP2D6 that results in extensive-, poor-,intermediate- and ultrarapid metabolizer phenotypes could contribute to large inter-individual variability in meclizine exposure.

Elimination

Meclizine has a plasma elimination half-life of about 5 to 6 hours in humans.

INDICATIONS AND USAGE

INDICATIONS

Based on a review of this drug by the National Academy of Sciences – National Research Council and/or other information, FDA has classified the indications as follows:

Effective: Management of nausea and vomiting, and dizziness associated with motion sickness.

Possibly Effective: Management of vertigo associated with diseases affecting the vestibular system.

Final classification of the less than effective indications required further investigation.

CONTRAINDICATIONS

Meclizine hydrochloride is contraindicated in individuals who have shown a previous hypersensitivity to it.

WARNINGS

Since drowsiness may, on occasion, occur with use of this drug, patients should be warned of this possibility and cautioned against driving a car or operating dangerous machinery.

Patients should avoid alcoholic beverages while taking the drug. Due to its potential anticholinergic action, this drug should be used with caution in patients with asthma, glaucoma, or enlargement of the prostate gland.

Usage in Children

Clinical studies establishing safety and effectiveness in children have not been done; therefore, usage is not recommended in children under 12 years of age.

Usage in Pregnancy

Pregnancy Category B. Reproduction studies in rats have shown cleft palates at 25 to 50 times the human dose. Epidemiological studies in pregnant women, however, do not indicate that meclizine increases the risk of abnormalities when administered during pregnancy. Despite the animal findings, it would appear that the possibility of fetal harm is remote. Nevertheless, meclizine, or any other medication, should be used during pregnancy only if clearly necessary.

PRECAUTIONS

The Meclizine Hydrochloride Tablets, 25 mg contain FD&C Yellow #5 (tartrazine) which may cause allergic-type reactions (including bronchial asthma) in certain susceptible individuals. Although the overall incidence of FD&C Yellow #5 (tartrazine) sensitivity in the general population is low, it is frequently seen in patients who also have aspirin hypersensitivity.

Nursing Mothers

It is not known whether this drug is excreted in human milk. Because many drugs are excreted in human milk, caution should be exercised when meclizine is administered to a nursing woman.

Hepatic Impairment

The effect of hepatic impairment on the pharmacokinetic of meclizine has not been evaluated. As meclizine undergoes metabolism, hepatic impairment may result in increased systemic exposure of the drug. Treatment with meclizine should be administered with caution in patients with hepatic impairment.

Renal Impairment

The effect of renal impairment on the pharmacokinetics of meclizine has not been evaluated. Due to a potential for drug/metabolite accumulation, meclizine should be administered with caution in patients with renal impairment and in the elderly as renal function generally declines with age.

Drug Interactions

There may be increased CNS depression when meclizine is administered concurrently with other CNS depressants, including alcohol, tranquilizers, and sedatives. (see WARNINGS).

Based on in-vitro evaluation, meclizine is metabolized by CYP2D6. Therefore there is a possibility for a drug interaction between meclizine and CYP2D6 inhibitors.

ADVERSE REACTIONS

Anaphylactoid reaction, drowsiness, dry mouth, headache, fatigue, vomiting and, on rare occasions, blurred vision have been reported.

DOSAGE AND ADMINISTRATION

Vertigo

For the control of vertigo associated with diseases affecting the vestibular system, the recommended dose is 25 to 100mg daily, in divided dosage, depending upon clinical response.

Motion Sickness: The initial dose of 25 to 50 mg meclizine hydrochloride, should be taken one hour prior to embarkation for protection against motion sickness. Thereafter, the dose may be repeated every 24 hours for the duration of the journey.

HOW SUPPLIED

Product: 50436-3988

NDC: 50436-3988-1 30 TABLET in a BOTTLE

NDC: 50436-3988-3 90 TABLET in a BOTTLE